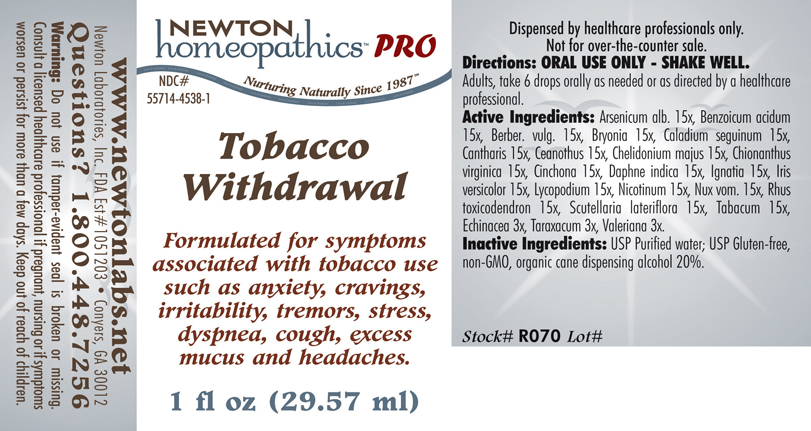 DRUG LABEL: Tobacco Withdrawal 
NDC: 55714-4538 | Form: LIQUID
Manufacturer: Newton Laboratories, Inc.
Category: homeopathic | Type: HUMAN PRESCRIPTION DRUG LABEL
Date: 20110601

ACTIVE INGREDIENTS: Arsenic Trioxide 15 [hp_X]/1 mL; Benzoic Acid 15 [hp_X]/1 mL; Berberis Vulgaris Root Bark 15 [hp_X]/1 mL; Bryonia Alba Root 15 [hp_X]/1 mL; Dieffenbachia Seguine 15 [hp_X]/1 mL; Lytta Vesicatoria 15 [hp_X]/1 mL; Ceanothus Americanus Leaf 15 [hp_X]/1 mL; Chelidonium Majus 15 [hp_X]/1 mL; Chionanthus Virginicus Bark 15 [hp_X]/1 mL; Cinchona Officinalis Bark 15 [hp_X]/1 mL; Daphne Odora Bark 15 [hp_X]/1 mL; Strychnos Ignatii Seed 15 [hp_X]/1 mL; Iris Versicolor Root 15 [hp_X]/1 mL; Lycopodium Clavatum Spore 15 [hp_X]/1 mL; Nicotine 15 [hp_X]/1 mL; Strychnos Nux-vomica Seed 15 [hp_X]/1 mL; Toxicodendron Pubescens Leaf 15 [hp_X]/1 mL; Scutellaria Lateriflora 15 [hp_X]/1 mL; Tobacco Leaf 15 [hp_X]/1 mL; Echinacea, Unspecified 3 [hp_X]/1 mL; Taraxacum Officinale 3 [hp_X]/1 mL; Valerian 3 [hp_X]/1 mL
INACTIVE INGREDIENTS: Alcohol

Tobacco Withdrawal

INDICATIONS & USAGE SECTION

Tobacco Withdrawal Formulated for symptoms associated with tobacco use such as anxiety, cravings, irritability, tremors, stress, dyspnea, cough, excess mucus and headaches.

DOSAGE & ADMINISTRATION SECTION

Directions: ORAL USE ONLY - SHAKE WELL. Adults, take 6 drops orally as needed or as directed by a healthcare professional.

ACTIVE INGREDIENT SECTION

Arsenicum alb. 15x, Benzoicum acidum 15x, Berber. vulg. 15x, Bryonia 15x, Caladium seguinum 15x, Cantharis 15x, Ceanothus 15x, Chelidonium majus 15x, Chionanthus virginica 15x, Cinchona 15x, Daphne indica 15x, Ignatia 15x, Iris versicolor 15x, Lycopodium 15x, Nicotinum 15x, Nux vom. 15x, Rhus toxicodendron 15x, Scutellaria lateriflora 15x, Tabacum 15x, Echinacea 3x, Taraxacum 3x, Valeriana 3x.

PURPOSE SECTION

Formulated for symptoms associated with tobacco use such as anxiety, cravings, irritability, tremors, stress, dyspnea, cough, excess mucus and headaches.

INACTIVE INGREDIENT SECTION

Inactive Ingredients: USP Purified Water; USP Gluten-free, non-GMO, organic cane dispensing alcohol 20%.

QUESTIONS? SECTION

www.newtonlabs.net Newton Laboratories, Inc. FDA Est # 1051203 - Conyers, GA 30012
Questions? 1.800.448.7256

WARNINGS SECTION

Warning: Do not use if tamper - evident seal is broken or missing. Consult a licensed healthcare professional if pregnant, nursing or if symptoms worsen or persist for more than a few days. Keep out of reach of children.

PREGNANCY OR BREAST FEEDING SECTION

Consult a licensed healthcare professional if pregnant, nursing or if symptoms worsen or persist for more than a few days

KEEP OUT OF REACH OF CHILDREN SECTION

Keep out of reach of children.